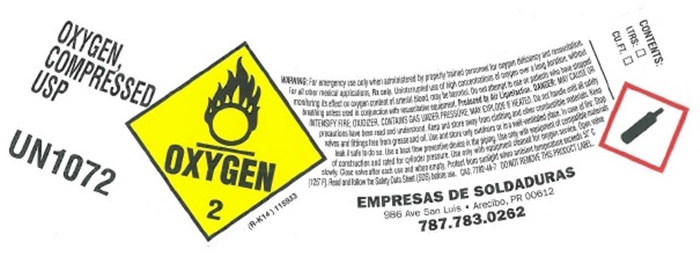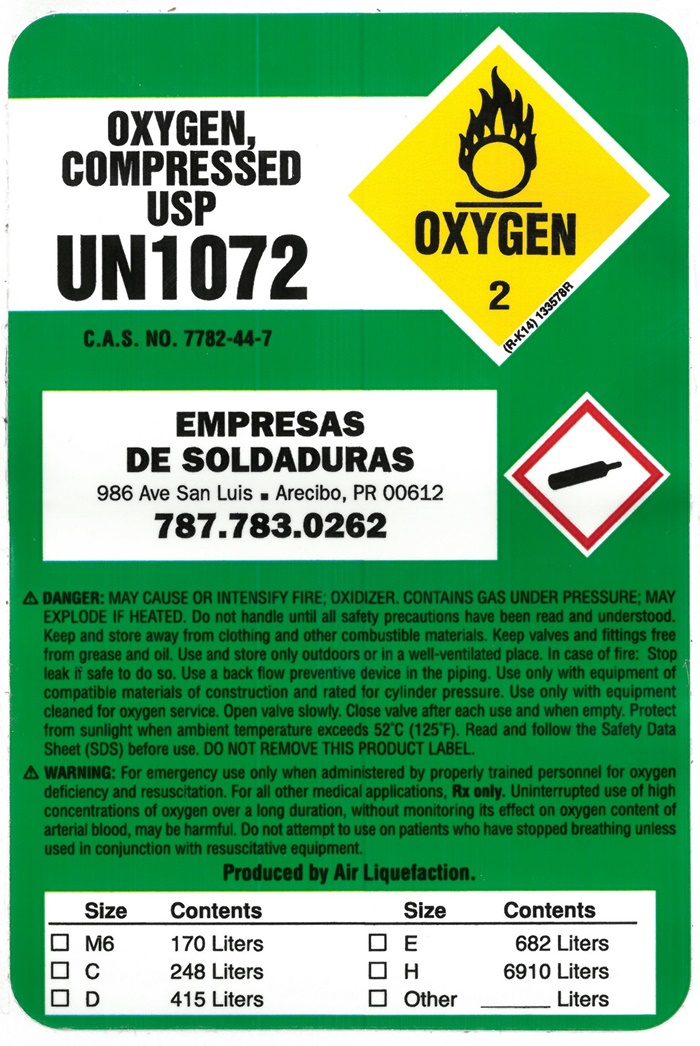 DRUG LABEL: Oxygen
NDC: 80421-100 | Form: GAS
Manufacturer: Empresas De Soldaduras
Category: prescription | Type: HUMAN PRESCRIPTION DRUG LABEL
Date: 20231018

ACTIVE INGREDIENTS: OXYGEN 1 L/1 L

Empresas de Soladuras - Oxygen

Oxygen

OXYGEN, COMPRESSED USP UN 1072

OXYGEN 2 (R-K14) 115933

WARNING: For emergency use only when administered by properly trained personnel for oxygen deficiency and resuscitation. For all other medical applications, Rx only. Uninterrupted use of high concentrations of oxygen over a long duration, without monitoring its effect on oxygen content of arterial blood, may be harmful. Do not attempt to use on patients who have stopped breathing unless used in conjunction with resuscitative equipment. DANGER: MAY CAUSE OR INTENSIFY FIRE; OXIDIZER. CONTAINS GAS UNDER PRESSURE; MAY EXPLODE IF HEATED. Do not handle until all safety precautions have been read and understood. Keep and store away from clothing and other combustible materials. Keep valves and fittings free from grease and oil. Use and store only outdoors or in a well-ventilated place. In case of fire: Stop leak if safe to do so. Use a backflow preventive device in the piping. Use only with equipment of compatible materials of construction and rated for cylinder pressure. Use only with equipment cleaned for oxygen service. Open valve slowly. Close valve after each use and when empty. Protect from sunlight when ambient temperature exceeds 52°C (125° F). Read and follow the Safety Data Sheet (SDS) before use. CAS 7782-44-7 DO NOT REMOVE THIS PRODUCT LABEL.

CONTENTS:

LTRS: ___

CU.FT. ___

EMPRESAS DE SOLDADURAS

986 Ave San Luis. • Arecibo, PR 00612

787.783.0262

Oxygen

OXYGEN, COMPRESSED USP

UN 1072

OXYGEN 2 (R-K14) 133578R

EMPRESAS DE SOLDADURAS

986 Ave San Luis. • Arecibo, PR 00612

787.783.0262

DANGER: MAY CAUSE OR INTENSIFY FIRE; OXIDIZER. CONTAINS GAS UNDER PRESSURE; MAY EXPLODE IF HEATED. Do not handle until all safety precautions have been read and understood. Keep and store away from clothing and other combustible materials. Keep valves and fittings free from grease and oil. Use and store only outdoors or in a well-ventilated place. In case of fire: Stop leak if safe to do so. Use a backflow preventive device in the piping. Use only with equipment of compatible materials of construction and rated for cylinder pressure. Use only with equipment cleaned for oxygen service. Open valve slowly. Close valve after each use and when empty. Protect from sunlight when ambient temperature exceeds 52°C (125° F). Read and follow the Safety Data Sheet (SDS) before use. CAS 7782-44-7 DO NOT REMOVE THIS PRODUCT LABEL.

WARNING: For emergency use only when administered by properly trained personnel for oxygen deficiency and resuscitation. For all other medical applications, Rx only. Uninterrupted use of high concentrations of oxygen over a long duration, without monitoring its effect on oxygen content of arterial blood, may be harmful. Do not attempt to use on patients who have stopped breathing unless used in conjunction with resuscitative equipment.

Produced by Air Liquefaction.

Size Contents Size Contents

□ M6 170 Liters □ E 682 Liters

□ C 248 Liters □ H 6910 Liters

□ D 415 Liters □ Other _____ Liters